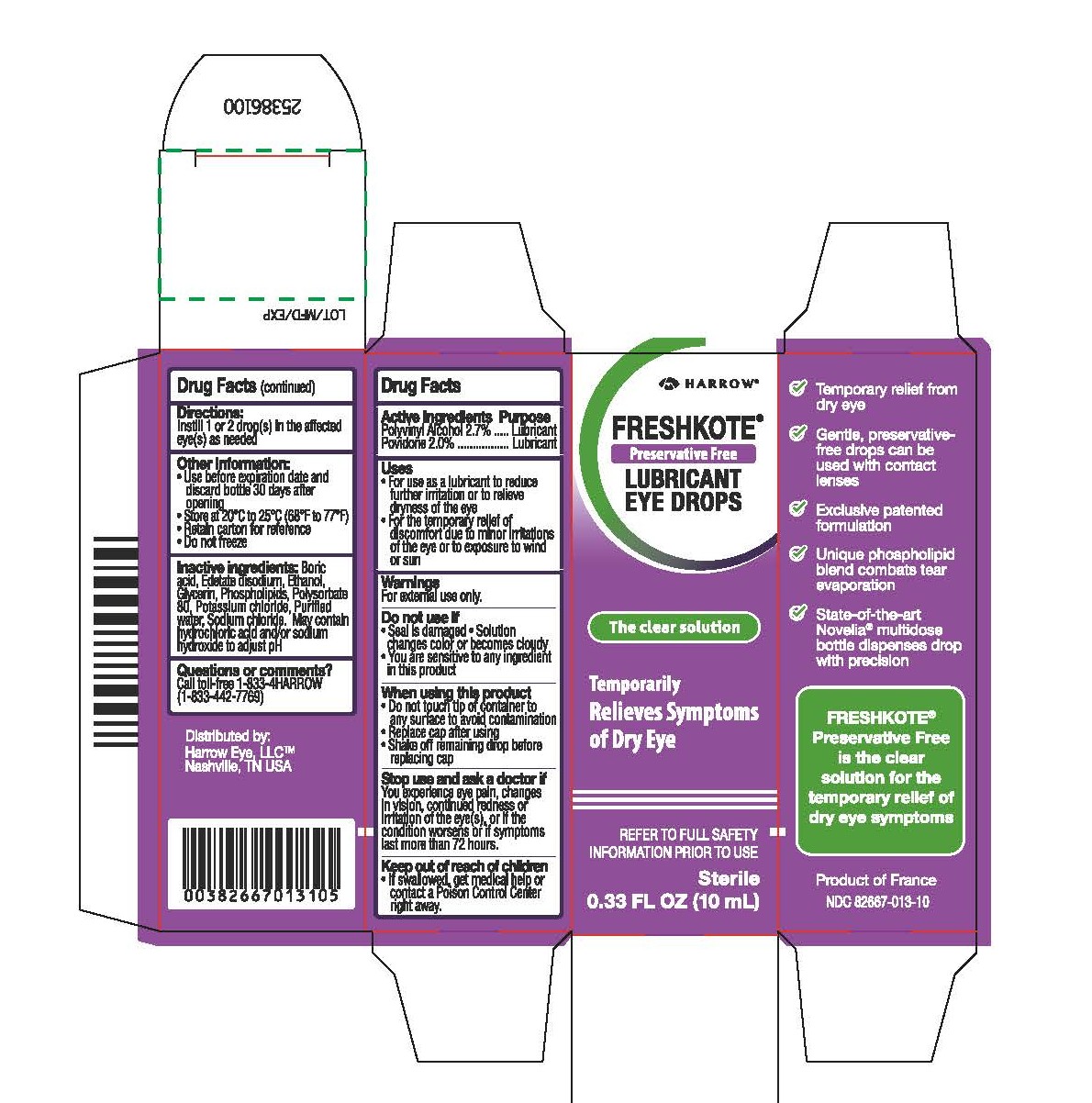 DRUG LABEL: FRESHKOTE PRESERVATIVE FREE LUBRICANT EYE DROPS
NDC: 82667-013 | Form: SOLUTION/ DROPS
Manufacturer: Harrow Eye, LLC
Category: otc | Type: HUMAN OTC DRUG LABEL
Date: 20250620

ACTIVE INGREDIENTS: POLYVINYL ALCOHOL, UNSPECIFIED 27 g/1000 mL; POVIDONE 20 g/1000 mL
INACTIVE INGREDIENTS: SODIUM CHLORIDE; EDETATE DISODIUM; POLYSORBATE 80; POTASSIUM CHLORIDE; BORIC ACID; WATER; ALCOHOL; EGG PHOSPHOLIPIDS; GLYCERIN

FRESHKOTE ®

Active Ingredients Purpose

Polyvinyl Alcohol 2.7%...... Lubricant

Povidone 2.0%...................Lubricant

Uses

For use as a lubricant to reduce further irritation or to relieve dryness of the eye
For the temporary relief of discomfort due to minor irritations of the eye or to exposure to wind or sun

Warnings

For external use only

Do not use if

Seal is damaged
Solution changes color or becomes cloudy
You are sensitive to any ingredient in this product

When using this product

Do not touch tip of container to any surface to avoid contamination
Replace cap after using
Shake off remaining drop before replacing cap

Stop use and ask a doctor if

You experience eye pain, changes in vision, continued redness or irritation of the eye(s), or if the condition worsens or if symptoms last more than 72 hours.

Keep out of reach of children

If swallowed, get medical help or contact a Poison Control Center right away

Directions:

Instill 1 or 2 drop(s) in the affected eye(s) as needed

Other information:

Use before expiration date and discard bottle 30 days after opening
Store at 20°C to 25°C (68°F to 77°F)
Retain carton for reference
Do not freeze

Inactive ingredients

Boric acid, Edetate disodium, Ethanol, Glycerin, Phospholipids, Polysorbate 80, Potassium chloride, Purified water, Sodium chloride. May contain hydrochloric acid and/or sodium hydroxide to adjust pH.

Questions or comments?

Call toll-free +1-833-4HARROW (+1-833-442-7769)

PURPOSE

FRESHKOTE® Preservative Free is the clear solution for the temporary relief of dry eye symptoms

PACKAGE LABEL

HARROW

FRESHKOTE®

Preservative Free

LUBRICANT EYE DROPS

The clear solution

Temporarily Relieves Symptoms of Dry Eye

REFER TO FULL SAFETY INFORMATION PRIOR TO USE

Sterile

0.33 FL OZ (10mL)

Temporary relief from dry eye

Gentle, preservative-free drops can be used with contact lenses

Exclusive patented formulation

Unique phospholipid blend combats tear evaporation

State-of-the-art Novelia® multidose bottle dispenses drop with precision

FRESHKOTE®

Preservative Free

is the clear

solution for the

temporary relief of

dry eye symptoms

Product of France

NDC 82667-013-10